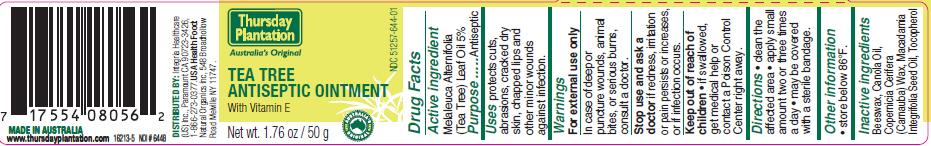 DRUG LABEL: Tea Tree Antiseptic
NDC: 51257-644 | Form: OINTMENT
Manufacturer: Integria Healthcare US Inc.
Category: otc | Type: HUMAN OTC DRUG LABEL
Date: 20110317

ACTIVE INGREDIENTS: TEA TREE OIL 2.5 g/50 g
INACTIVE INGREDIENTS: YELLOW WAX; CANOLA OIL; CARNAUBA WAX; MACADAMIA OIL

ACTIVE INGREDIENT

Melaleuca Alternifolia (Tea Tree) Leaf Oil 5%

PURPOSE

Antiseptic

INDICATIONS AND USAGE

protects cuts, abrasions, cracked dry skin, chapped lips and other minor wounds against infection

WARNINGS

For external use only

ASK DOCTOR

In case of deep or puncture wounds, animal bites, or serious burns, consult a doctor.

Stop use and ask a doctor if redness, irritation or pain persists or increases, or if infection occurs.

Keep out of reach of children, if swallowed get medical help or contact a Poison Control Center right away.

DOSAGE AND ADMINISTRATION

- clean the affected area
- apply small amount two or three times a day
- may be covered with a sterile bandage

STORAGE AND HANDLING

store below 86 degrees F

INACTIVE INGREDIENT

Beeswax, Canola Oil, Copernicia Cerifera (Carnauba) Wax, Macadamia Integrifolia Seed Oil, Tocopherol